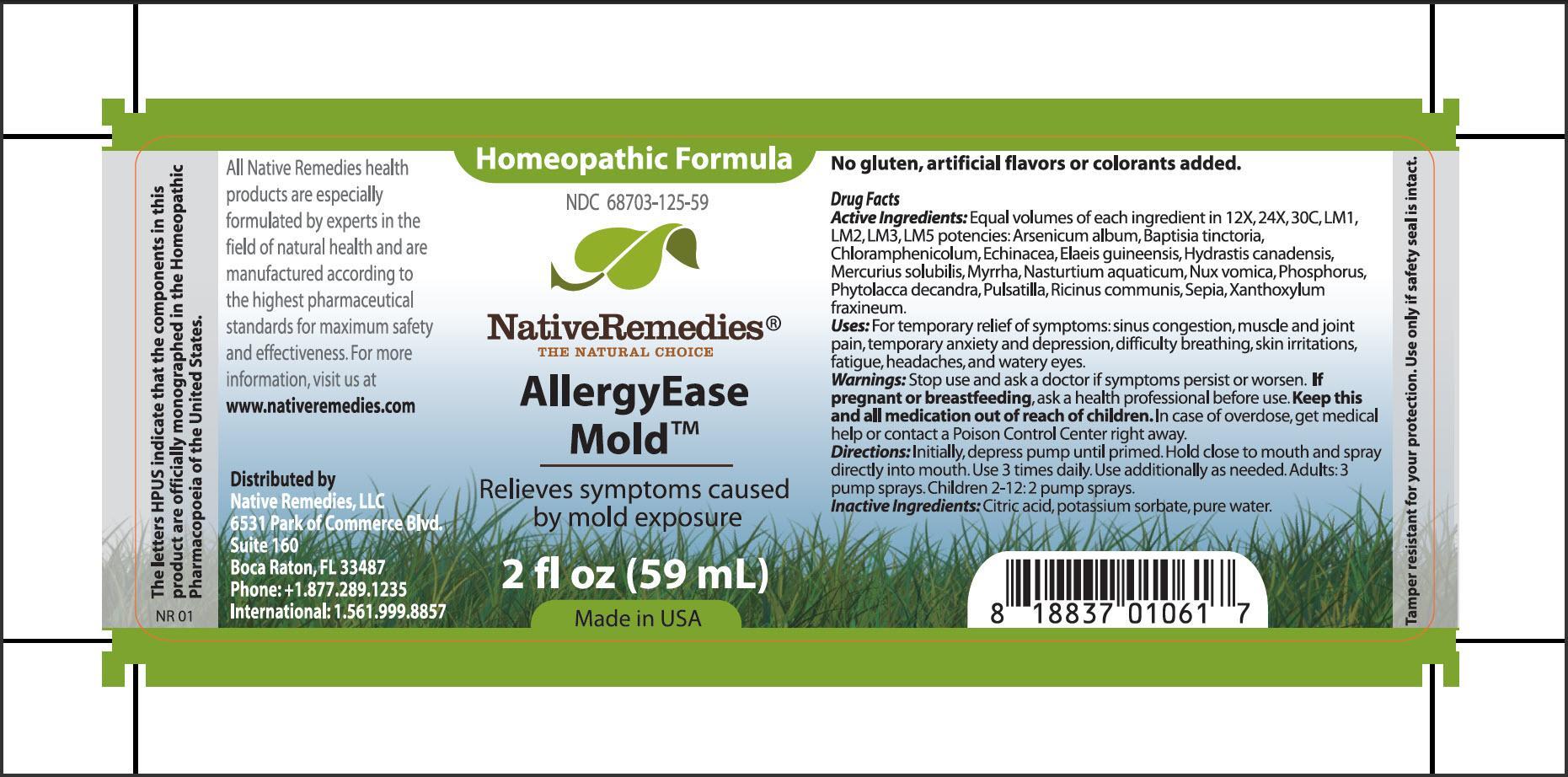 DRUG LABEL: AllergyEase Mold
NDC: 68703-125 | Form: SPRAY
Manufacturer: Native Remedies, LLC
Category: homeopathic | Type: HUMAN OTC DRUG LABEL
Date: 20130729

ACTIVE INGREDIENTS: ARSENIC TRIOXIDE 12 [hp_X]/59 mL; BAPTISIA TINCTORIA ROOT 12 [hp_X]/59 mL; CHLORAMPHENICOL 12 [hp_X]/59 mL; ECHINACEA, UNSPECIFIED 12 [hp_X]/59 mL; ELAEIS GUINEENSIS FRUIT 12 [hp_X]/59 mL; GOLDENSEAL 12 [hp_X]/59 mL; MERCURIUS SOLUBILIS 12 [hp_X]/59 mL; MYRRH 12 [hp_X]/59 mL; NASTURTIUM OFFICINALE  12 [hp_X]/59 mL; STRYCHNOS NUX-VOMICA SEED 12 [hp_X]/59 mL; PHOSPHORUS 12 [hp_X]/59 mL; PHYTOLACCA AMERICANA ROOT 12 [hp_X]/59 mL; PULSATILLA VULGARIS 12 [hp_X]/59 mL; RICINUS COMMUNIS SEED 12 [hp_X]/59 mL; SEPIA OFFICINALIS JUICE 12 [hp_X]/59 mL; ZANTHOXYLUM AMERICANUM BARK 12 [hp_X]/59 mL
INACTIVE INGREDIENTS: CITRIC ACID MONOHYDRATE; POTASSIUM SORBATE; WATER

AllergyEase Mold

PURPOSE

Relieves symptoms caused by mold exposure

Drug Facts
Active Ingredients: Equal volumes of each ingredient in 12X, 24X, 30C, LM1, LM2, LM3, LM5 potencies: Arsenicum album, Baptisia tinctoria, Chloramphenicolum, Echinacea, Elais guineensis, Hydrastis canadensis, Mercuris solubilis, Myrrha, Nasturtium aquaticum, Nux vomica, Phosphorus, Phytolacca decandra, Pulsatilla, Ricinus communis, Sepia, Xanthoxylum fraxineum

INDICATIONS AND USAGE

Uses:For temporary relief of symptoms: sinus congestion, muscle and join pain, temporary anxiety and depression, difficulty breathing, skin irritations, fatigue, headaches, and watery eyes

WARNINGS

Warnings: Stop use and ask a doctor if symptoms persist or worsen

PREGNANCY OR BREAST FEEDING

If pregnant or breastfeeding, ask a health professional before use

KEEP OUT OF REACH OF CHILDREN

Keep this and all medication out of reach of children

OVERDOSAGE

In case of overdose, get medical help or contact a Poison Control Center right away

DOSAGE AND ADMINISTRATION

Directions: Initially, depress pump until primed. Hold close to mouth and spray directly into mouth. Use 3 times daily. Use additionally as needed. Adults: 3 pump sprays. Children 2-12: 2 pump sprays

Inactive Ingredients: Citric acid, potassium sorbate, pure water

PATIENT COUNSELING INFORMATION

The letter HPUS indicate that the components in this product are officially monographed in the Homeopathic Pharmacopoeia of the United States.

All Native Remedies health products are especially formulated by experts in the field of natural health and are manufactured according to the highest pharmaceutical standards for maximum safety and effectiveness. For more information, visit us at www.nativeremedies.com

Distributed by
Native Remedies, LLC
6531 Park of Commerce Blvd.
Suite 160
Boca Raton, FL 33487
Phone: +1.877.289.1235
International: 1.561.999.8857

No gluten, artificial flavors or colorants added

STORAGE AND HANDLING

Tamper resistant for your protection. Use only if safety seal is intact